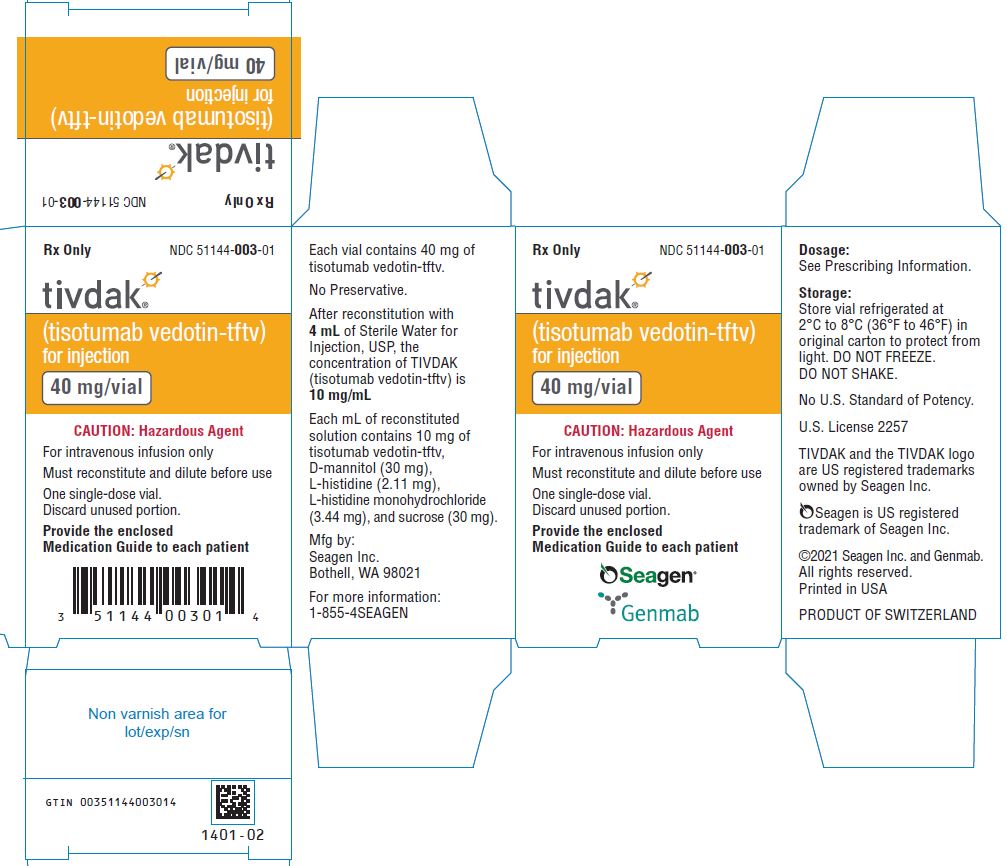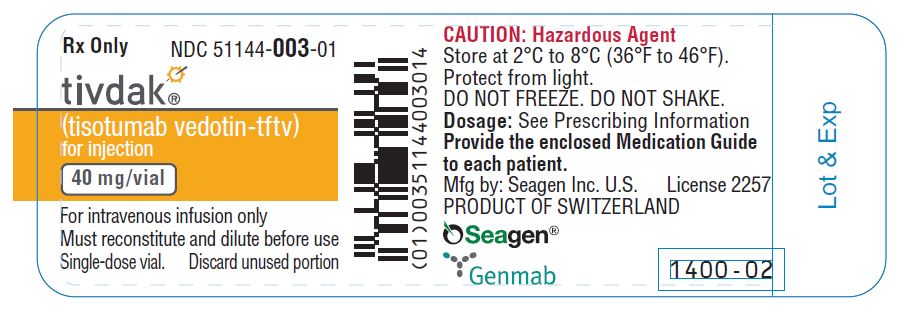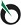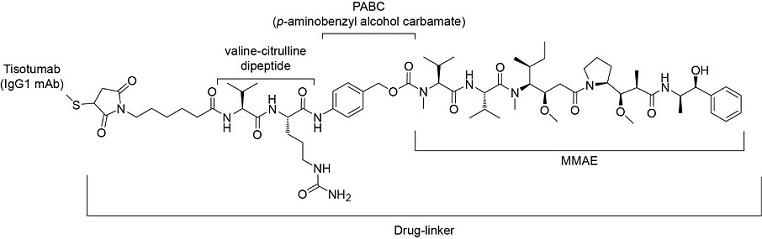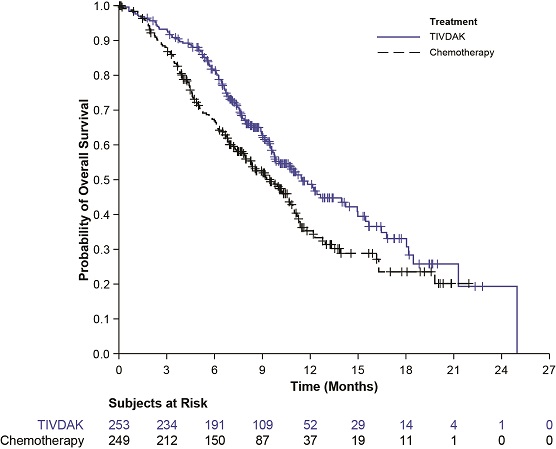 DRUG LABEL: TIVDAK
NDC: 51144-003 | Form: INJECTION, POWDER, FOR SOLUTION
Manufacturer: SEAGEN INC.
Category: prescription | Type: HUMAN PRESCRIPTION DRUG LABEL
Date: 20251120

ACTIVE INGREDIENTS: Tisotumab Vedotin 40 mg/4 mL
INACTIVE INGREDIENTS: Mannitol; Histidine Monohydrochloride Monohydrate; Sucrose; Histidine

HIGHLIGHTS OF PRESCRIBING INFORMATION

These highlights do not include all the information needed to use TIVDAK safely and effectively. See full prescribing information for TIVDAK.
TIVDAK® (tisotumab vedotin-tftv) for injection, for intravenous use
Initial U.S. Approval: 2021

WARNING: OCULAR TOXICITY

See full prescribing information for complete boxed warning.

- TIVDAK can cause severe ocular toxicities resulting in changes in vision, including severe vision loss and corneal ulceration. (5.1)
- Conduct an ophthalmic exam, including an assessment of ocular symptoms, visual acuity, and slit lamp exam of the anterior segment of the eye prior to initiation of TIVDAK, prior to every cycle for the first nine cycles, and as clinically indicated. (2.2, 5.1)
- Adhere to the required premedication and eye care before, during, and after infusion. (2.2)
- Withhold TIVDAK until improvement and resume, reduce the dose, or permanently discontinue, based on severity. (2.3, 5.1)

1 INDICATIONS AND USAGE

TIVDAK is a tissue factor-directed antibody and microtubule inhibitor conjugate indicated for the treatment of adult patients with recurrent or metastatic cervical cancer with disease progression on or after chemotherapy. (1)

2 DOSAGE AND ADMINISTRATION

- For intravenous infusion only. Do not administer TIVDAK as an intravenous push or bolus. Do not mix with, or administer as an infusion with, other medicinal products. (2.4)
- The recommended dose of TIVDAK is 2 mg/kg (up to a maximum of 200 mg) given as an intravenous infusion over 30 minutes every 3 weeks until disease progression or unacceptable toxicity. (2.1)

3 DOSAGE FORMS AND STRENGTHS

For Injection: 40 mg as a lyophilized cake or powder in a single-dose vial for reconstitution. (3)

4 CONTRAINDICATIONS

None. (4)

5 WARNINGS AND PRECAUTIONS

- Peripheral neuropathy: Monitor patients for new or worsening peripheral neuropathy. Withhold, reduce the dose, or permanently discontinue TIVDAK based on severity. (2.3, 5.2)
- Hemorrhage: Monitor patients for signs and symptoms of hemorrhage. Withhold, reduce the dose, or permanently discontinue TIVDAK based on severity. (2.3, 5.3)
- Pneumonitis: Severe, life-threatening, or fatal pneumonitis may occur. Withhold TIVDAK for persistent or recurrent Grade 2 pneumonitis and consider dose reduction. Permanently discontinue TIVDAK for Grade 3 or 4 pneumonitis. (2.3, 5.4)
- Severe Cutaneous Adverse Reactions: Severe cutaneous adverse reactions, including events of fatal or life-threatening Stevens-Johnson syndrome (SJS), can occur in patients treated with TIVDAK. Immediately withhold TIVDAK for suspected severe cutaneous adverse reactions, including SJS. Permanently discontinue TIVDAK for confirmed Grade 3 or 4 severe cutaneous adverse reactions, including SJS. (2.3, 5.5)
- Embryo-fetal toxicity: TIVDAK can cause fetal harm. Advise of the potential risk to a fetus and to use effective contraception. (5.6, 8.1, 8.3)

6 ADVERSE REACTIONS

The most common (≥25%) adverse reactions, including laboratory abnormalities, were hemoglobin decreased, peripheral neuropathy, conjunctival adverse reactions, nausea, fatigue, aspartate aminotransferase increased, epistaxis, alopecia, alanine aminotransferase increased, and hemorrhage. (6.1)
To report SUSPECTED ADVERSE REACTIONS, contact Seagen Inc. at 1-855-4SEAGEN or FDA at 1-800-FDA-1088 or www.fda.gov/medwatch.

7 DRUG INTERACTIONS

Strong CYP3A4 Inhibitors: Closely monitor for TIVDAK adverse reactions. (7.1)

8 USE IN SPECIFIC POPULATIONS

- Moderate or severe hepatic impairment: Exposure to MMAE and adverse reactions are increased. Avoid use. (8.6)
- Lactation: Advise women not to breastfeed. (8.2)

FULL PRESCRIBING INFORMATION

WARNING: OCULAR TOXICITY

- TIVDAK can cause severe ocular toxicities resulting in changes in vision, including severe vision loss, and corneal ulceration. [see Warnings and Precautions (5.1)].
- Conduct an ophthalmic exam, including an assessment of ocular symptoms, visual acuity, and slit lamp exam of the anterior segment of the eye prior to initiation of TIVDAK, prior to every cycle for the first nine cycles, and as clinically indicated. [see Dosage and Administration (2.2) and Warnings and Precautions (5.1)].
- Adhere to the required premedication and eye care before, during, and after infusion. [see Dosage and Administration (2.2)].
- Withhold TIVDAK until improvement and resume, reduce the dose, or permanently discontinue, based on severity [see Dosage and Administration (2.3), Warnings and Precautions (5.1)].

1 INDICATIONS AND USAGE

TIVDAK® is indicated for the treatment of adult patients with recurrent or metastatic cervical cancer with disease progression on or after chemotherapy.

2 DOSAGE AND ADMINISTRATION

2.1 Recommended Dosage

The recommended dose of TIVDAK is 2 mg/kg (up to a maximum of 200 mg for patients ≥100 kg) administered as an intravenous infusion over 30 minutes every 3 weeks until disease progression or unacceptable toxicity.

2.2 Premedication and Required Eye Care

Adhere to the following recommendations to reduce the risk of ocular adverse reactions [see Warnings and Precautions (5.1)].

- Ophthalmic exam by eye care provider: Conduct an ophthalmic exam prior to initiation of TIVDAK, prior to every cycle for the first nine cycles, and as clinically indicated. The ophthalmic exam should include visual acuity, slit lamp exam of the anterior segment of the eye, and an assessment of normal eye movement.
- Topical corticosteroid eye drops: Instruct patients to administer one drop in each eye prior to each infusion and to continue to administer eye drops in each eye three times daily for 72 hours after each infusion. The initial prescription and all renewals of any corticosteroid medication should be made only after examination with a slit lamp.
- Topical ocular vasoconstrictor drops: Administer in each eye immediately prior to each infusion of TIVDAK.
- Cold packs: Use cooling eye pads during each infusion of TIVDAK.
- Topical lubricating eye drops: Instruct patients to administer for the duration of therapy and for 30 days after the last dose of TIVDAK.
- Contact lenses: Advise patients to avoid wearing contact lenses for the entire duration of therapy unless advised by their eye care provider.

2.3 Dosage Modifications for Adverse Reactions

The recommended TIVDAK dose reduction schedule is provided in Table 1.

Table 1: Dosage Reduction Schedule
 | TIVDAK Dose Level
Starting dose | 2 mg/kg (up to a maximum of 200 mg for patients ≥100 kg)
First dose reduction | 1.3 mg/kg (up to a maximum of 130 mg for patients ≥100 kg)
Second dose reduction | 0.9 mg/kg [Permanently discontinue in patients who cannot tolerate 0.9 mg/kg] (up to a maximum of 90 mg for patients ≥100 kg)

The recommended dose modifications for adverse reactions are provided in Table 2.

Table 2: Dosage Modifications for Adverse Reactions
Adverse Reaction | Severity | Occurrence | TIVDAK Dose Modification
Keratitis [Refer patients to an eye care provider promptly for an assessment of new or worsening ocular symptoms.]; [see Warnings and Precautions (5.1)] | Nonconfluent superficial keratitis | Any | Monitor.
Keratitis [Refer patients to an eye care provider promptly for an assessment of new or worsening ocular symptoms.]; [see Warnings and Precautions (5.1)] | Confluent superficial keratitis, a corneal epithelial defect, or a 3 line or more loss in best corrected visual acuity | First occurrence | Withhold dose until resolution, or improvement to nonconfluent superficial keratitis, then resume treatment at the next lower dose level.
Keratitis [Refer patients to an eye care provider promptly for an assessment of new or worsening ocular symptoms.]; [see Warnings and Precautions (5.1)] | Confluent superficial keratitis, a corneal epithelial defect, or a 3 line or more loss in best corrected visual acuity | Second occurrence | Permanently discontinue.
Keratitis [Refer patients to an eye care provider promptly for an assessment of new or worsening ocular symptoms.]; [see Warnings and Precautions (5.1)] | Ulcerative keratitis or perforation | Any | Permanently discontinue.
Conjunctival or corneal scarring or symblepharon; [see Warnings and Precautions (5.1)] | Any scarring or symblepharon | Any | Permanently discontinue.
Conjunctivitis and other ocular adverse reactions; [see Warnings and Precautions (5.1)] | Nonconfluent superficial punctate conjunctival defects, mild vasodilation | Any | Monitor.
Conjunctivitis and other ocular adverse reactions; [see Warnings and Precautions (5.1)] | Confluent superficial punctate conjunctival defects, moderate to severe vasodilation | First occurrence | Withhold dose until resolution or improvement to nonconfluent superficial punctate conjunctival defects, mild vasodilation, then resume treatment at the same dose.
Conjunctivitis and other ocular adverse reactions; [see Warnings and Precautions (5.1)] | Confluent superficial punctate conjunctival defects, moderate to severe vasodilation | Second occurrence | Withhold dose until resolution or improvement to nonconfluent superficial punctate conjunctival defects, mild vasodilation, then resume treatment at the next lower dose level. If no resolution or improvement to nonconfluent superficial punctate conjunctival defects, mild vasodilation, permanently discontinue.
Conjunctivitis and other ocular adverse reactions; [see Warnings and Precautions (5.1)] | Confluent superficial punctate conjunctival defects, moderate to severe vasodilation | Third occurrence | Permanently discontinue.
Conjunctivitis and other ocular adverse reactions; [see Warnings and Precautions (5.1)] | Conjunctival ulcer, conjunctival neovascularization, or fibrovascular scarring | Any | Permanently discontinue.
Peripheral Neuropathy; [see Warnings and Precautions (5.2)] | Grade 2 | Any (initial or worsening of pre-existing condition) | Withhold dose until Grade ≤1, then resume treatment at the next lower dose level.
Peripheral Neuropathy; [see Warnings and Precautions (5.2)] | Grade 3 or 4 | Any | Permanently discontinue.
Hemorrhage; [see Warnings and Precautions (5.3)] | Any grade pulmonary or CNS | Any | Permanently discontinue.
Hemorrhage; [see Warnings and Precautions (5.3)] | Grade 2 in any other location | Any | Withhold until resolved, then resume treatment at the same dose.
Hemorrhage; [see Warnings and Precautions (5.3)] | Grade 3 in any other location | First occurrence | Withhold dose until resolved, then resume treatment at the same dose.
Hemorrhage; [see Warnings and Precautions (5.3)] | Grade 3 in any other location | Second occurrence | Permanently discontinue.
Hemorrhage; [see Warnings and Precautions (5.3)] | Grade 4 in any other location | Any | Permanently discontinue.
Pneumonitis; [see Warnings and Precautions (5.4)] | Grade 2 | Any | Withhold dose until Grade ≤1 for persistent or recurrent pneumonitis, consider resuming treatment at next lower dose level.
Pneumonitis; [see Warnings and Precautions (5.4)] | Grade 3 or 4 | Any | Permanently discontinue.
Severe cutaneous adverse reactions (including Stevens-Johnson syndrome (SJS)); [see Warnings and Precautions (5.5)] | Suspected (any grade) | Any | Immediately withhold dose and consult a specialist to confirm the diagnosis.
Severe cutaneous adverse reactions (including Stevens-Johnson syndrome (SJS)); [see Warnings and Precautions (5.5)] | Confirmed Grade 3 or 4 | Any | Permanently discontinue.

2.4 Instructions for Preparation and Administration

- Administer TIVDAK as an intravenous infusion only.
- TIVDAK is a hazardous drug. Follow applicable special handling and disposal procedures^1.
- DO NOT administer TIVDAK as an intravenous push or bolus.
- DO NOT mix TIVDAK with, or administer as an infusion with, other medicinal products.

Use appropriate aseptic technique for reconstitution and preparation of dosing solutions. Prior to administration, the TIVDAK vial is reconstituted with Sterile Water for Injection, USP. The reconstituted solution is subsequently diluted in an intravenous infusion bag containing one of the following: 5% Dextrose Injection USP, 0.9% Sodium Chloride Injection, USP, or Lactated Ringer’s Injection, USP.

Reconstitution in Single-dose Vial

1. Calculate the recommended dose based on the patient’s weight to determine the number of vials needed.
2. Reconstitute each 40 mg vial with 4 mL of Sterile Water for Injection, USP, resulting in 10 mg/mL TIVDAK.
3. Slowly swirl each vial until the contents are completely dissolved. Allow the reconstituted vial(s) to settle. DO NOT SHAKE THE VIAL. Do not expose to direct sunlight.
4. Parenteral drug products should be inspected visually for particulate matter and discoloration prior to administration, whenever solution and container permit. The reconstituted solution should be clear to slightly opalescent, colorless to brownish-yellow and free of visible particles. Discard any vial with visible particles or discoloration.
5. Based upon the calculated dose amount, the reconstituted solution from the vial(s) should be added to the infusion bag immediately. This product does not contain a preservative. If not used immediately, reconstituted vials may be stored for up to 24 hours in refrigeration at 2°C to 8°C (36 °F to 46 °F) or at room temperature up to 25°C (77°F) for up to a maximum of 8 hours prior to dilution. DO NOT FREEZE. Do not expose to direct sunlight. Discard unused vials with reconstituted solution beyond the recommended storage time.

Dilution in Infusion Bag

1. Withdraw the calculated dose amount of reconstituted solution from the vial(s) and transfer into an infusion bag.
2. Dilute TIVDAK with one of the following: 5% Dextrose Injection, USP, 0.9% Sodium Chloride Injection, USP or Lactated Ringer's Injection, USP. The infusion bag size should allow enough diluent to achieve a final concentration of 0.7 mg/mL to 2.4 mg/mL TIVDAK.
3. Mix diluted solution by gentle inversion. DO NOT SHAKE THE BAG. Do not expose to direct sunlight.
4. Visually inspect the infusion bag for any particulate matter or discoloration prior to use. The reconstituted solution should be clear to slightly opalescent, colorless to brownish-yellow and free of visible particles. Discard the infusion bag if particulate matter or discoloration is observed.
5. Discard any unused portion left in the single-dose vials.

Administration

1. Confirm administration of steroid and vasoconstrictor eye drops [see Dosage and Administration (2.2)].
2. Apply cold packs fully over the eyes following administration of the vasoconstrictor eye drops. Change cold packs as needed throughout infusion to ensure eye area remains cold during the entire infusion [see Dosage and Administration (2.2)].
3. Immediately administer the infusion over 30 minutes through an intravenous line containing a 0.2 µm in-line filter.
4. If the infusion is not administered immediately, store the diluted TIVDAK solution in refrigeration as specified in Table 3. Discard if storage time exceeds these limits. DO NOT FREEZE. Once removed from refrigeration, complete administration of the diluted infusion solution of TIVDAK within 4 hours (including infusion time).

Table 3: Diluted TIVDAK Solution Refrigeration Storage Conditions
Diluent Used to Prepare Solution for Infusion | Diluted TIVDAK Solution Storage Conditions (Including Infusion Time)
5% Dextrose Injection, USP | Up to 24 hours at 2°C to 8°C (36°F to 46°F)
0.9% Sodium Chloride Injection, USP | Up to 18 hours at 2°C to 8°C (36°F to 46°F)
Lactated Ringer’s Injection, USP | Up to 12 hours at 2°C to 8°C (36°F to 46°F)

3 DOSAGE FORMS AND STRENGTHS

For Injection: 40 mg of tisotumab vedotin-tftv as a white to off-white lyophilized cake or powder in a single-dose vial for reconstitution.

4 CONTRAINDICATIONS

None.

5 WARNINGS AND PRECAUTIONS

5.1 Ocular Adverse Reactions

TIVDAK can cause severe ocular adverse reactions, including conjunctivitis, keratopathy (keratitis, punctate keratitis, and ulcerative keratitis), and dry eye (increased lacrimation, eye pain, eye discharge, pruritus, irritation, and foreign body sensation), that may lead to changes in vision and/or corneal ulceration.

Ocular adverse reactions occurred in 55% of patients with cervical cancer treated with TIVDAK across clinical trials. The most common ocular adverse reactions were conjunctivitis (32%), dry eye (24%), keratopathy (17%), and blepharitis (5%). Grade 3 ocular adverse reactions occurred in 3.3% of patients, including severe ulcerative keratitis in 1.2% of patients. Nine patients (2.1%) experienced ulcerative keratitis (including one with perforation requiring corneal transplantation), six (1.4%) conjunctival ulcer, four (0.9%) corneal erosion, two (0.5%) conjunctival erosion, and two (0.5%) symblepharon.

The median time to onset of the first ocular adverse reaction was 1.2 months (range, 0-17.1). Of the patients who experienced ocular events, 59% had complete resolution and 31% had partial improvement (defined as a decrease in severity by one or more grades from the worst grade) at last follow up. Ocular adverse reactions led to permanent discontinuation of TIVDAK in 6% of patients with cervical cancer.

In innovaTV 301, 8 (3.2%) patients experienced delayed ocular adverse reactions occurring more than 30 days after discontinuation of TIVDAK. These adverse reactions included 3 patients with ulcerative keratitis, and one patient (each) with keratitis, punctate keratitis and corneal erosion, blepharitis and conjunctival hyperemia, conjunctival scar, and conjunctivitis and xerophthalmia.

Refer patients to an eye care provider to conduct an ophthalmic exam prior to initiation of TIVDAK, prior to every cycle for the first nine cycles, and as clinically indicated. The exam should include visual acuity, slit lamp exam of the anterior segment of the eye, and an assessment of normal eye movement and ocular signs or symptoms which include dry or irritated eyes, eye secretions or blurry vision.

Adhere to the required premedication and eye care before, during, and after infusion to reduce the risk of ocular adverse reactions [see Dosage and Administration (2.2)].

Monitor for ocular toxicity and promptly refer patients to an eye care provider for any new or worsening ocular signs and symptoms. Withhold, reduce, or permanently discontinue TIVDAK based on the severity or persistence of the ocular adverse reaction [see Dosage and Administration (2.3)].

5.2 Peripheral Neuropathy

Peripheral neuropathy occurred in 39% of patients with cervical cancer treated with TIVDAK across clinical trials; 6% of patients experienced Grade 3 peripheral neuropathy. Peripheral neuropathy adverse reactions included peripheral sensory neuropathy (23%), peripheral neuropathy (5%), paresthesia (3.8%), peripheral sensorimotor neuropathy (3.3%), muscular weakness (2.8%), and peripheral motor neuropathy (2.4%). One patient with another tumor type treated with TIVDAK at the recommended dose developed Guillain-Barre syndrome.

The median time to onset of peripheral neuropathy was 2.4 months (range, 0-11.3). Of the patients who experienced peripheral neuropathy, 18% had complete resolution and 21% had partial improvement (defined as a decrease in severity by one or more grades from the worst grade) at last follow up. Peripheral neuropathy led to discontinuation of TIVDAK in 7% of patients with cervical cancer.

Monitor patients for signs and symptoms of neuropathy, such as paresthesia, tingling or a burning sensation, neuropathic pain, muscle weakness, or dysesthesia. For patients experiencing new or worsening peripheral neuropathy, withhold dose, then dose reduce, or permanently discontinue TIVDAK based on the severity of peripheral neuropathy [see Dosage and Administration (2.3)].

5.3 Hemorrhage

Hemorrhage occurred in 51% of patients with cervical cancer treated with TIVDAK across clinical trials. The most common all grade hemorrhage adverse reaction was epistaxis (33%). Grade 3 hemorrhage occurred in 4% of patients.

The median time to onset of hemorrhage was 0.3 months (range, 0-10.4). Of the patients who experienced hemorrhage, 71% had complete resolution and 12% had partial resolution (defined as a decrease in severity by one or more grades from the worst grade) at last follow-up.

Monitor patients for signs and symptoms of hemorrhage. For patients experiencing pulmonary or CNS hemorrhage, permanently discontinue TIVDAK. For grade ≥2 hemorrhage in any other location, withhold until bleeding has resolved, blood hemoglobin is stable, there is no bleeding diathesis that could increase the risk of continuing therapy, and there is no anatomical or pathologic condition that can increase the risk of hemorrhage recurrence. After resolution, either resume treatment or permanently discontinue TIVDAK [see Dosage and Administration (2.3)].

5.4 Pneumonitis

Severe, life-threatening, or fatal pneumonitis can occur in patients treated with antibody drug conjugates containing vedotin including TIVDAK. Among patients with cervical cancer treated with TIVDAK across clinical trials, 4 patients (0.9%) experienced pneumonitis, including 1 patient who had a fatal outcome.

Monitor patients for pulmonary symptoms indicative of pneumonitis. Symptoms may include hypoxia, cough, dyspnea or interstitial infiltrates on radiologic exams. Infectious, neoplastic, and other causes for such symptoms should be excluded through appropriate investigations.

Withhold TIVDAK for patients who develop persistent or recurrent Grade 2 pneumonitis and consider dose reduction. Permanently discontinue TIVDAK in all patients with Grade 3 or 4 pneumonitis [see Dosage and Administration (2.3)].

5.5 Severe Cutaneous Adverse Reactions

Severe cutaneous adverse reactions, including events of fatal or life-threatening SJS, can occur in patients treated with TIVDAK. Severe cutaneous adverse reactions occurred in 1.6% of patients with cervical cancer treated with TIVDAK across clinical trials. Grade ≥3 severe cutaneous adverse reactions occurred in 0.5% of patients, including 1 patient who had a fatal outcome.

Monitor patients for signs or symptoms of severe cutaneous adverse reactions, which include target lesions, worsening skin reactions, blistering or peeling of the skin, painful sores in mouth, nose, throat, or genital area, fever or flu-like symptoms, and swollen lymph nodes. If signs or symptoms of severe cutaneous adverse reactions occur, withhold TIVDAK until the etiology of the reaction has been determined. Early consultation with a specialist is recommended to ensure greater diagnostic accuracy and appropriate management. Permanently discontinue TIVDAK for confirmed Grade 3 or 4 severe cutaneous adverse reactions, including SJS [see Dosage and Administration (2.3)].

5.6 Embryo-Fetal Toxicity

Based on the mechanism of action and findings in animals, TIVDAK can cause fetal harm when administered to a pregnant woman. The small molecule component of TIVDAK, MMAE, administered to rats caused adverse developmental outcomes, including embryo-fetal mortality and structural abnormalities, at exposures below those occurring clinically at the recommended dose.

Advise patients of the potential risk to a fetus. Advise females of reproductive potential to use effective contraception during treatment with TIVDAK and for 2 months after the last dose. Advise male patients with female partners of reproductive potential to use effective contraception during treatment with TIVDAK and for 4 months after the last dose [see Use in Specific Populations (8.1, 8.3), and Clinical Pharmacology (12.1)].

6 ADVERSE REACTIONS

The following serious adverse reactions are described elsewhere in the labeling:

- Ocular Adverse Reactions [see Boxed Warning, Warnings and Precautions (5.1)]
- Peripheral Neuropathy [see Warnings and Precautions (5.2)]
- Hemorrhage [see Warnings and Precautions (5.3)]
- Pneumonitis [see Warnings and Precautions (5.4)]
- Severe Cutaneous Adverse Reactions [see Warnings and Precautions (5.5)]

6.1 Clinical Trials Experience

Because clinical trials are conducted under widely varying conditions, adverse reaction rates observed in the clinical trials of a drug cannot be directly compared to rates in the clinical trials of another drug and may not reflect the rates observed in practice.

The data in the WARNINGS AND PRECAUTIONS section reflect exposure to TIVDAK in 425 patients with recurrent or metastatic cervical cancer who received at least one dose of TIVDAK at 2 mg/kg intravenously every 3 weeks in innovaTV 301, innovaTV 204, innovaTV 201 (NCT02001623), innovaTV 202 (NCT02552121), innovaTV 203 (NCT03245736), and innovaTV 206 (NCT03913741). The median duration of treatment with TIVDAK was 3.7 months (range: 0.4-40.2). In this pooled safety population, the most common (≥25%) adverse reactions, including laboratory abnormalities, were hemoglobin decreased (45%), peripheral neuropathy (39%), conjunctival adverse reactions (38%), nausea (37%), fatigue (36%), aspartate aminotransferase increased (33%), epistaxis (33%), alopecia (31%), alanine aminotransferase increased (30%), and hemorrhage (28%).

The data described in this section reflect exposure to TIVDAK from innovaTV 301 and innovaTV 204.

innovaTV 301

The safety of TIVDAK was evaluated in an open-label, randomized study in patients with recurrent or metastatic cervical cancer with disease progression on or after systemic therapy [see Clinical Studies (14.1)]. A total of 250 patients received TIVDAK 2 mg/kg every 3 weeks until disease progression or unacceptable toxicity. The median duration of treatment with TIVDAK was 3.7 months (range: 0.4-19).

Serious adverse reactions occurred in 33% of patients receiving TIVDAK. The most common (≥2%) serious adverse reactions were urinary tract infection (4.8%), small intestinal obstruction (2.4%), sepsis (2%), abdominal pain (2%), and hemorrhage (2%). Fatal adverse reactions occurred in 1.6% of patients who received TIVDAK, including acute kidney injury (0.4%), pneumonia (0.4%), sepsis (0.4%) and Stevens-Johnson syndrome (0.4%).

Adverse reactions leading to permanent discontinuation occurred in 15% of patients receiving TIVDAK; the most common (≥3%) adverse reactions leading to permanent discontinuation were peripheral neuropathy (6%) and ocular adverse reactions (6%).

Adverse reactions leading to dose interruption occurred in 39% of patients receiving TIVDAK; the most common (≥3%) adverse reactions leading to dose interruption were ocular adverse reactions (16%) and peripheral neuropathy (6%).

Adverse reactions leading to dose reduction occurred in 30% of patients receiving TIVDAK; the most common (≥3%) adverse reactions leading to dose reduction were peripheral neuropathy (10%) and ocular adverse reactions (10%). The ocular adverse reactions included conjunctival disorders (4.8%), keratopathy (4%), and dry eye (0.8%).

The most common (≥25%) adverse reactions, including laboratory abnormalities, in patients receiving TIVDAK were hemoglobin decreased, peripheral neuropathy, conjunctival adverse reactions, aspartate aminotransferase increased, nausea, alanine aminotransferase increased, fatigue, sodium decreased, epistaxis, and constipation.

Table 4 summarizes the all grade and Grade 3-4 adverse reactions from innovaTV 301.

Table 4: Adverse Reactions (≥10%) in Patients Who Received TIVDAK in innovaTV 301
Adverse Reaction | TIVDAK N=250 |  | Chemotherapy N=239
Adverse Reaction | All Grades | Grade 3-4 | All Grades | Grade 3-4
Adverse Reaction | % | % | % | %
Nervous system disorders
Peripheral neuropathy [Peripheral neuropathy includes peripheral sensory neuropathy, paresthesia, muscular weakness, peripheral sensorimotor neuropathy, peripheral motor neuropathy, neurotoxicity, gait disturbance, neuralgia, hypoaesthesia, neuropathy peripheral, and skin burning sensation] | 38 | 6 | 4.2 | 0.4
Eye disorders
Conjunctival adverse reactions [Conjunctival adverse reactions includes conjunctivitis, conjunctivitis bacterial, conjunctivitis viral, episcleritis, ocular hyperemia, conjunctival hemorrhage, conjunctival hyperemia, conjunctival ulcer, conjunctivitis allergic, conjunctival disorder, symblepharon, conjunctival erosion, conjunctival oedema, conjunctivochalasis, and conjunctival scar] | 37 | 0 | 1.7 | 0
Corneal adverse reactions [Corneal adverse reactions includes keratitis, punctate keratitis, corneal erosion, ulcerative keratitis, corneal degeneration, corneal opacity, and keratopathy] | 21 | 3.2 | 0 | 0
Dry eye [Dry eye includes dry eye, eye discharge, eye pruritus, eye pain, eye irritation, and lacrimation increased] | 21 | 0 | 1.7 | 0
Gastrointestinal disorders
Nausea [Nausea includes nausea and retching] | 33 | 0.4 | 40 | 2.1
Constipation | 25 | 1.2 | 16 | 0
Diarrhea [Diarrhea includes diarrhea and gastroenteritis] | 22 | 1.6 | 15 | 1.3
Abdominal Pain [Abdominal pain includes abdominal pain, abdominal pain upper, abdominal discomfort, and abdominal pain lower] | 18 | 4 | 15 | 2.5
Vomiting | 18 | 1.6 | 18 | 1.3
General
Fatigue [Fatigue includes fatigue and asthenia] | 28 | 6 | 32 | 6
Pyrexia | 17 | 0.4 | 21 | 0.8
Pruritus | 10 | 0.4 | 2.9 | 0
Vascular disorders
Epistaxis | 26 | 0 | 2.5 | 0
Hemorrhage [Hemorrhage includes hematuria, vaginal hemorrhage, rectal hemorrhage, hemoptysis, anal hemorrhage, hemorrhage, gastrointestinal hemorrhage, hemorrhagic shock, lower gastrointestinal hemorrhage, gingival bleeding, tumor hemorrhage, intra-abdominal hemorrhage, gastric hemorrhage, genital hemorrhage, uterine hemorrhage, urinary tract hemorrhage, hemorrhoidal hemorrhage] | 21 | 2 | 11 | 2.5
Metabolism and nutrition disorders
Decreased appetite | 24 | 0.8 | 18 | 0.4
Decreased weight | 10 | 0.4 | 5 | 0
Skin and subcutaneous tissue disorders
Alopecia | 24 | 0 | 2.9 | 0
Rash [Rash includes rash maculo-papular, eczema, rash macular, rash pustular, dermatitis acneiform, erythema, rash, urticaria, dermatitis, and rash erythematous] | 17 | 1.6 | 16 | 1.3
Infections
Urinary tract infection [Urinary tract infection includes urinary tract infection, pyelonephritis acute, cystitis, and urinary tract infection bacterial] | 16 | 5 | 18 | 8

Clinically relevant adverse reactions in <10% of patients who received TIVDAK in innovaTV 301 include periorbital adverse reactions (9%) and intestinal obstruction (4.4%, including small bowel, large bowel, and malignant gastrointestinal obstruction).

Table 5 summarizes the laboratory abnormalities in innovaTV 301.

Table 5: Select Laboratory Abnormalities (≥10%) That Worsened from Baseline In Patients Who Received TIVDAK in innovaTV 301
 | TIVDAK [The denominator used to calculate the rate varied from 206 to 244 based on the number of patients with a baseline value and at least one post-treatment value.] |  | Chemotherapy
 | All Grades (%) | Grades 3 or 4 (%) | All Grades (%) | Grades 3-4 (%)
Hematology
Hemoglobin decreased | 41 | 7 | 70 | 23
Neutrophils decreased | 16 | 3.3 | 39 | 17
Chemistry
Aspartate aminotransferase increased | 34 | 2.5 | 32 | 0.4
Alanine aminotransferase increased | 30 | 3.3 | 35 | 2.6
Sodium decreased | 27 | 0.4 | 27 | 0.4
Creatinine increased | 23 | 2 | 26 | 2.2
Coagulation
Activated partial thromboplastin time prolonged | 16 | 1.9 | 17 | 0.5

innovaTV 204

The safety of TIVDAK was evaluated in a single arm study in patients (n=101) with recurrent or metastatic cervical cancer with disease progression on or after chemotherapy [see Clinical Studies (14.1)]. Patients received TIVDAK 2 mg/kg every 3 weeks until disease progression or unacceptable toxicity. The median duration of treatment was 4.2 months (range: 0.7-16).

Serious adverse reactions occurred in 43% of patients. The most common (≥3%) serious adverse reactions were ileus (6%), hemorrhage (5%), pneumonia (4%), peripheral neuropathy, sepsis, constipation, and pyrexia (each 3%). Fatal adverse reactions occurred in 4% of patients who received TIVDAK, including septic shock (1%), pneumonitis (1%), sudden death (1%), and multisystem organ failure (1%).

Adverse reactions leading to permanent discontinuation occurred in 13% of patients receiving TIVDAK; the most common (≥3%) adverse reactions leading to permanent discontinuation were peripheral neuropathy (5%) and corneal adverse reactions (4%).

Adverse reactions leading to dose interruption occurred in 47% of patients; the most (≥3%) common adverse reactions leading to dose interruption were peripheral neuropathy (8%), conjunctival adverse reactions (4%), and hemorrhage (4%).

Adverse reactions leading to dose reduction occurred in 23% of patients; the most common (≥3%) adverse reactions leading to dose reduction were conjunctival adverse reactions (9%) and corneal adverse reactions (8%).

The most common (≥25%) adverse reactions, including laboratory abnormalities, were hemoglobin decreased, fatigue, lymphocytes decreased, nausea, peripheral neuropathy, alopecia, epistaxis, conjunctival adverse reactions, hemorrhage, leukocytes decreased, creatinine increased, dry eye, prothrombin international normalized ratio increased, activated partial thromboplastin time prolonged, diarrhea, and rash.

Table 6 summarizes the all grade and Grade 3-4 adverse reactions from innovaTV 204.

Table 6: Adverse Reactions (≥10%) in Patients Who Received TIVDAK in innovaTV 204
Adverse Reaction | TIVDAK N=101
Adverse Reaction | All Grades % | Grade 3-4 %
General
Fatigue [Fatigue includes fatigue and asthenia] | 50 | 7
Pyrexia | 16 | 1
Pruritus | 13 | 1
Gastrointestinal disorders
Nausea [Nausea includes nausea and retching] | 41 | 0
Diarrhea [Diarrhea includes diarrhea, gastroenteritis, and colitis] | 25 | 2
Constipation | 23 | 2
Abdominal pain [Abdominal pain includes abdominal pain, abdominal pain upper, abdominal pain lower, abdominal distention and abdominal discomfort] | 23 | 1
Vomiting | 17 | 2
Nervous system disorders
Peripheral neuropathy [Peripheral neuropathy includes neuropathy peripheral, peripheral sensorimotor neuropathy, polyneuropathy, peripheral sensory neuropathy, paresthesia, hypoesthesia, burning sensation, neuralgia, sensory loss, peripheral motor neuropathy, muscular weakness, gait disturbance, and hyperesthesia] | 39 | 7
Skin and subcutaneous tissue disorders
Alopecia | 39 | 0
Rash [Rash includes rash, rash maculo-papular, rash macular, dermatitis acneiform, dermatitis allergic, and erythema] | 25 | 0
Vascular disorders
Epistaxis | 39 | 0
Hemorrhage [Hemorrhage includes vaginal hemorrhage, hematuria, rectal hemorrhage, cystitis hemorrhagic, lower gastrointestinal hemorrhage, urinary bladder hemorrhage, hematochezia, anal hemorrhage, gingival bleeding, post procedural hemorrhage, radiation associated with hemorrhage, metrorrhagia, large intestinal hemorrhage, paranasal sinus hemorrhage, and hemoptysis] | 32 | 6
Eye disorders
Conjunctival adverse reactions [Conjunctival adverse reactions includes conjunctivitis, conjunctival abrasion, conjunctival erosion, conjunctival hyperemia, conjunctival scar, noninfective conjunctivitis, ocular hyperemia, and conjunctival hemorrhage] | 37 | 0
Dry eye [Dry eye includes dry eye and lacrimation increased] | 29 | 0
Corneal adverse reactions [Corneal adverse reactions includes keratitis, punctate keratitis, ulcerative keratitis, corneal erosion, corneal scar, keratopathy, and corneal bleeding] | 21 | 3
Periorbital adverse reactions [Periorbital adverse reactions includes blepharitis, meibomianitis, eye pruritus, entropion, trichiasis, chalazion, and meibomian gland dysfunction] | 16 | 0
Musculoskeletal and connective tissue disorders
Myalgia [Myalgia includes myalgia, musculoskeletal discomfort, and musculoskeletal pain] | 21 | 0
Arthralgia | 16 | 0
Pain in extremity [Pain in extremity includes pain in extremity and limb discomfort] | 13 | 1
Metabolism and nutrition disorders
Decreased appetite | 16 | 1
Infections
Urinary tract infection [Urinary tract infection includes urinary tract infection, urinary tract infection bacterial, and cystitis] | 14 | 2
Investigations
Weight decreased | 12 | 0

Clinically relevant adverse reactions in <10% of patients who received TIVDAK in innovaTV 204 included venous thrombosis (3%), pulmonary embolism (3%), and pneumonitis (2%).

Table 7 summarizes the laboratory abnormalities in innovaTV 204.

Table 7: Select Laboratory Abnormalities (≥10%) That Worsened from Baseline In Patients Who Received TIVDAK in innovaTV 204
Laboratory Abnormality | TIVDAK [The denominator used to calculate the rate varied from 96 to 101 based on the number of patients with a baseline value and at least one post-treatment value.]
Laboratory Abnormality | All Grades (%) | Grade 3 or 4 (%)
Hematology
Hemoglobin decreased | 52 | 7
Neutrophils decreased | 21 | 3
Chemistry
Creatinine increased | 29 | 4.1
Alanine aminotransferase increased | 24 | 0
Aspartate aminotransferase increased | 18 | 0
Sodium decreased | 20 | 0
Alkaline phosphatase increased | 17 | 0
Creatinine kinase increased | 16 | 2.1
Magnesium decreased | 17 | 2.1
Coagulation
Prothrombin international normalized ratio increased | 26 | 0
Activated partial thromboplastin time prolonged | 26 | 2

7 DRUG INTERACTIONS

7.1 Effects of Other Drugs on TIVDAK

Strong CYP3A4 Inhibitors
MMAE is a CYP3A4 substrate. Concomitant use of TIVDAK with strong CYP3A4 inhibitors may increase unconjugated MMAE exposure [see Clinical Pharmacology (12.3)], which may increase the risk of TIVDAK adverse reactions. Closely monitor patients for adverse reactions of TIVDAK when used concomitantly with strong CYP3A4 inhibitors.

8 USE IN SPECIFIC POPULATIONS

8.1 Pregnancy

Risk Summary

Based on the mechanism of action and findings in animals, TIVDAK can cause fetal harm when administered to a pregnant woman [see Clinical Pharmacology (12.1)]. There are no available human data on TIVDAK use in pregnant women to inform a drug-associated risk. In an animal reproduction study, administration of the small molecule component of TIVDAK, MMAE, to pregnant rats during organogenesis caused embryo-fetal mortality and structural abnormalities at exposures below the clinical exposure at the recommended dose (see Data). Advise patients of the potential risk to a fetus.

The background risk of major birth defects and miscarriage for the indicated population is unknown. In the U.S. general population, the estimated background risk of major birth defects and miscarriage in clinically recognized pregnancies is 2%-4% and 15%-20%, respectively.

Data
Animal Data

No embryo-fetal development studies in animals have been performed with tisotumab vedotin-tftv. In an embryo-fetal development study in pregnant rats, administration of two intravenous doses of MMAE, the small molecule component of TIVDAK, on gestational days 6 and 13 caused embryo-fetal mortality and structural abnormalities, including protruding tongue, malrotated limbs, gastroschisis, and agnathia compared to controls at a dose of 0.2 mg/kg (approximately 0.5-fold the human area under the curve [AUC] at the recommended dose).

8.2 Lactation

Risk Summary

There are no data on the presence of tisotumab vedotin-tftv in human milk, the effects on the breastfed child, or the effects on milk production. Because of the potential for serious adverse reactions in a breastfed child, advise lactating women not to breastfeed during treatment with TIVDAK and for 3 weeks after the last dose.

8.3 Females and Males of Reproductive Potential

TIVDAK can cause fetal harm when administered to a pregnant woman [see Use in Specific Populations (8.1)].

Pregnancy testing

Verify pregnancy status in females of reproductive potential prior to initiating TIVDAK treatment.

Contraception

Females

Advise females of reproductive potential to use effective contraception during treatment with TIVDAK and for 2 months after the last dose.

Males

Advise male patients with female partners of reproductive potential to use effective contraception during treatment with TIVDAK and for 4 months after the last dose.

Infertility

Females

Based on findings in animal studies with MMAE-containing antibody-drug conjugates (ADCs), TIVDAK may impair female fertility. The effect on fertility is reversible [see Nonclinical Toxicology (13.1)].

Males

Based on findings from animal studies, TIVDAK may impair male fertility [see Nonclinical Toxicology (13.1)].

8.4 Pediatric Use

Safety and effectiveness of TIVDAK in pediatric patients have not been established.

Nonclinical studies of tisotumab vedotin-tftv suggest a lack of anti-tumor activity and penetrance to brain based on limited in vivo data from tissue factor (TF)-expressing subcutaneous or orthotopic pediatric models of high‑grade gliomas/glioblastomas (HGG/GBM) and diffuse intrinsic pontine glioma (DIPG).

8.5 Geriatric Use

Of the 425 patients with cervical cancer treated with TIVDAK across clinical trials, 14% were ≥65 years of age and 2.4% were ≥75 years of age. Grade ≥3 adverse reactions occurred in 60% of patients ≥65 years and in 55% of patients <65 years. Drug was discontinued due to an adverse reaction in 25% of patients ≥65 years and in 13% of patients <65 years. Clinical studies of TIVDAK did not include sufficient numbers of patients 65 years of age and older to determine whether they respond differently from younger patients.

8.6 Hepatic Impairment

Avoid use of TIVDAK in patients with moderate or severe hepatic impairment [aspartate aminotransferase (AST) > 3 x upper limit of normal (ULN) or total bilirubin > 1.5 × ULN] [see Clinical Pharmacology (12.3)].

In patients with mild hepatic impairment (total bilirubin ≤ ULN and AST >ULN or total bilirubin > 1 to 1.5 × ULN and any AST), closely monitor patients for adverse reactions of TIVDAK, but no dosage adjustment in the starting dose of TIVDAK is recommended.

11 DESCRIPTION

Tisotumab vedotin-tftv is a Tissue Factor (TF) directed antibody drug conjugate (ADC) comprised of a human anti-TF IgG1-kappa antibody conjugated to the microtubule-disrupting agent monomethyl auristatin E (MMAE) via a protease-cleavable vc (valine-citrulline) linker. The monoclonal antibody is produced in a mammalian cell line (Chinese hamster ovary). MMAE and the linker are produced by chemical synthesis. Each monoclonal antibody molecule carries an average of 4 MMAE molecules. Tisotumab vedotin-tftv has an approximate molecular weight of 153 kDa. The chemical structure is as follows:

Figure 1. Structural Formula

TIVDAK (tisotumab vedotin-tftv) for injection, is provided as a sterile, preservative-free, white to off-white lyophilized cake or powder in a single-dose vial for infusion after dilution. Following reconstitution with 4 mL of Sterile Water for Injection, a clear to slightly opalescent, colorless to brownish-yellow solution containing 10 mg/mL tisotumab vedotin-tftv is produced [see Dosage and Administration (2.3)]. Each mL of reconstituted solution contains 10 mg of tisotumab vedotin-tftv, d-mannitol (30 mg), l-histidine (2.11 mg), l-histidine monohydrochloride (3.44 mg), and sucrose (30 mg), at pH 6.0.

12 CLINICAL PHARMACOLOGY

12.1 Mechanism of Action

Tisotumab vedotin-tftv is a tissue factor (TF)-directed antibody drug conjugate (ADC). The antibody is a human IgG1 directed against cell surface TF. TF is the primary initiator of the extrinsic blood coagulation cascade. The small molecule, MMAE, is a microtubule-disrupting agent, attached to the antibody via a protease-cleavable linker. Nonclinical data suggests that the anticancer activity of tisotumab vedotin-tftv is due to the binding of the ADC to TF expressing cancer cells, followed by internalization of the ADC-TF complex, and release of MMAE via proteolytic cleavage. MMAE disrupts the microtubule network of actively dividing cells, leading to cell cycle arrest and apoptotic cell death. In vitro, tisotumab vedotin-tftv also mediates antibody-dependent cellular phagocytosis and antibody-dependent cellular cytotoxicity.

12.2 Pharmacodynamics

Tisotumab vedotin-tftv exposure-response relationships and the time course of pharmacodynamics response have not been fully characterized.

Cardiac Electrophysiology

At the recommended dose, tisotumab vedotin-tftv had no large mean effect on QTc prolongation (>20 msec).

12.3 Pharmacokinetics

Table 8 summarizes the exposure parameters of tisotumab vedotin-tftv and unconjugated MMAE (the cytotoxic component of tisotumab vedotin-tftv) following administration of one 3-week cycle of tisotumab vedotin-tftv 2 mg/kg to patients. Tisotumab vedotin-tftv concentrations peaked near the end of the infusion, while unconjugated MMAE concentrations peaked approximately 2 to 3 days after tisotumab vedotin-tftv dosing. Tisotumab vedotin-tftv Cmax increased proportionally, while AUC0-last increased in a more than dose-proportional manner, after a single dose ranging from 0.3–2.2 mg/kg (0.15 to 1.1 times the approved recommended dose). There was no accumulation of tisotumab vedotin-tftv and unconjugated MMAE. Steady-state concentrations of tisotumab vedotin-tftv and unconjugated MMAE were reached after 1 treatment cycle.

Table 8. Exposure Parameters of Tisotumab Vedotin-tftv and Unconjugated MMAE
 | Tisotumab Vedotin-tftv Mean (± SD) | Unconjugated MMAE Mean (± SD)
Cmax | 40.8 (8.12) μg/mL | 5.91 (4.2) ng/mL
AUC | 57.5 (13.4) day*μg/mL | 50 (35.8) day*ng/mL
Cmax=maximum concentration, AUC = area under the concentration-time curve from time 0 to 21 days (3 weeks)

Distribution

The tisotumab vedotin-tftv steady state volume of distribution is 7.83 (%CV: 19.1) L. Plasma protein binding of MMAE ranged from 68% to 82%, in vitro.

Elimination

The median terminal half-life of tisotumab vedotin-tftv and unconjugated MMAE is 4.04 (range: 2.26-7.25) days and 2.56 (range: 1.81-4.10) days, respectively. The linear clearance of tisotumab vedotin-tftv and unconjugated MMAE was 1.54 (%CV: 28.8) L/day and 45.9 (%CV: 61.1) L/day, respectively. Elimination of MMAE appeared to be limited by its rate of release from tisotumab vedotin-tftv.

Metabolism

Tisotumab vedotin-tftv is expected to undergo catabolism to small peptides, amino acids, unconjugated MMAE, and unconjugated MMAE-related catabolites. Tisotumab vedotin-tftv releases unconjugated MMAE via proteolytic cleavage, and unconjugated MMAE is primarily metabolized by CYP3A4 in vitro.

Excretion

The excretion of tisotumab vedotin-tftv is not fully characterized. Following a single-dose of another ADC that contains MMAE, 17% of the total MMAE administered was recovered in feces and 6% in urine over a 1-week period, primarily as unchanged drug. A similar excretion profile of MMAE is expected after tisotumab vedotin-tftv administration.

Specific Populations

No clinically significant differences in the pharmacokinetics of tisotumab vedotin-tftv were observed based on age (21 to 81 years), sex, race (white vs non-white) or ethnicity (Hispanic or Latino vs non-Hispanic or non-Latino). No clinically significant differences in exposures of tisotumab vedotin-tftv and unconjugated MMAE were observed in patients with mild to moderate renal impairment (CLcr 30 to < 90 mL/min using the Cockcroft-Gault equation) compared to patients with normal renal function. The effect of severe renal impairment (CLcr 15 to < 30 mL/min) or end-stage renal disease with or without dialysis on pharmacokinetics of tisotumab vedotin-tftv and unconjugated MMAE is unknown.

Patients with Hepatic Impairment

Unconjugated MMAE exposures were 37% higher, but there were no clinically significant differences in exposures of tisotumab vedotin-tftv in patients with mild hepatic impairment compared to patients with normal hepatic function. The effect of moderate or severe hepatic impairment or liver transplantation on the pharmacokinetics of tisotumab vedotin-tftv or unconjugated MMAE is unknown.

Drug Interaction Studies

Clinical Studies

No clinical studies evaluating the drug-drug interaction potential of tisotumab vedotin-tftv have been conducted. To characterize the drug-drug interaction potential of unconjugated MMAE, clinical studies with another ADC that contains MMAE are described below, and similar effects on tisotumab vedotin-tftv and unconjugated MMAE exposures are expected with concomitant use of TIVDAK.

There were no clinically significant differences in midazolam (sensitive CYP3A4 substrate) pharmacokinetics when used concomitantly with another ADC that contains MMAE.

Strong CYP3A4 Inhibitors: Ketoconazole (strong CYP3A4 inhibitor) used concomitantly with another ADC that contains MMAE increased unconjugated MMAE Cmax by 25% and AUC by 34%, with no change in ADC exposure.

Strong CYP3A4 Inducers: Rifampin (strong CYP3A4 inducer) used concomitantly with another ADC that contains MMAE decreased unconjugated MMAE Cmax by 44% and AUC by 46%, with no change in ADC exposure.

In Vitro Studies

Cytochrome P450 (CYP) Enzymes: MMAE does not inhibit CYP1A2, CYP2B6, CYP2C8, CYP2C9, CYP2C19, or CYP2D6. MMAE did not induce any major CYP450 enzymes in human hepatocytes.

Transporter Systems: MMAE is a substrate of P-glycoprotein (P-gp), but not an inhibitor of P-gp.

12.6 Immunogenicity

The observed incidence of anti-drug antibodies (ADA) is highly dependent on the sensitivity and specificity of the assay. Differences in assay methods preclude meaningful comparisons of the incidence of ADA in the studies described below with the incidence of ADA in other studies, including those of TIVDAK or of other tisotumab vedotin products.

In patients with recurrent or metastatic cervical cancer who were treated with TIVDAK 2 mg/kg every 3 weeks for up to 19 months (innovaTV 301) and 40 months (innovaTV 204), the incidence of anti-tisotumab vedotin-tftv antibody formation was 5.7% (12/211) and 5.4% (5/93), respectively. The incidence of neutralizing anti-tisotumab vedotin-tftv antibody formation was 0% (0/211) in innovaTV 301 using cell-based assay, and the incidence was 2.2% (2/93) in innovaTV 204 using Enzyme-linked Immunosorbent Assay (ELISA)-based assay. Given the low number of patients who developed anti-tisotumab vedotin-tftv antibodies, no conclusions can be drawn concerning a potential effect of immunogenicity on pharmacokinetics, efficacy or safety.

13 NONCLINICAL TOXICOLOGY

13.1 Carcinogenesis, Mutagenesis, Impairment of Fertility

Carcinogenicity studies in animals have not been performed with tisotumab vedotin-tftv or MMAE.

MMAE was positive for genotoxicity in the in vivo rat bone marrow micronucleus study through an aneugenic mechanism. MMAE was not mutagenic in the bacterial reverse mutation (Ames) assay or the L5178 TK+/- mouse lymphoma forward mutation assay.

Fertility studies with tisotumab vedotin-tftv or MMAE have not been conducted. However, results of a repeat-dose toxicity study in monkeys indicate the potential for tisotumab vedotin-tftv to impair male reproductive function and fertility.

In a repeat-dose toxicology study conducted in monkeys for 13 weeks, doses ≥1 mg/kg tisotumab vedotin-tftv (≥0.6 times the human exposure [AUC] at the recommended dose) resulted in decreased testicular size and seminiferous tubule atrophy, reduction or absence in sperm count, and decreased sperm motility. Findings of sperm absence and decreased motility did not reverse by the end of the recovery period at doses ≥3 mg/kg (≥1.7 times the human exposure [AUC] at the recommended dose).

MMAE-containing ADCs have been associated with adverse ovarian effects when administered to sexually immature animals. Adverse effects included decrease in, or absence of, secondary and tertiary ovarian follicles after weekly administration to cynomolgus monkeys in studies of 4-week duration. These effects showed a trend towards recovery 6 weeks after the end of dosing; no changes were observed in primordial follicles.

14 CLINICAL STUDIES

14.1 Recurrent or Metastatic Cervical Cancer

innovaTV 301

The efficacy of TIVDAK was evaluated in innovaTV 301 (NCT04697628), an open-label, active-controlled, multicenter, randomized trial that enrolled 502 patients with recurrent or metastatic cervical cancer who had received one or two prior systemic therapy regimens in the recurrent or metastatic setting, including chemotherapy with or without bevacizumab and/or an anti-PD-(L)1 agent. Patients were excluded if they had active ocular surface disease, any prior episode of cicatricial conjunctivitis or ocular SJS, Grade ≥2 peripheral neuropathy, or clinically significant bleeding issues or risks.

Patients were randomized (1:1) to receive either TIVDAK 2 mg/kg intravenously every 3 weeks (n=253) or investigator’s choice of chemotherapy (n=249) consisting of topotecan, vinorelbine, gemcitabine, irinotecan or pemetrexed, until unacceptable toxicity or disease progression. Randomization was stratified by prior treatment with bevacizumab (yes or no), prior anti-PD-(L)1 therapy (yes or no), region (US, Europe, or Other), and ECOG performance status (0 or 1).

Patients were treated until disease progression or unacceptable toxicity. Tumor response assessments were performed every 6 weeks for the first 30 weeks and every 12 weeks thereafter.

The major efficacy outcome measure was overall survival (OS). Additional efficacy outcome measures were progression free survival (PFS) and confirmed objective response rate (ORR) as assessed by investigator using RECIST v1.1.

The median age was 50 years (range: 26 to 80); 49% were White, 36% were Asian, 10% were not reported, 3% were American Indian or Alaskan Native, and 2% were Black; 20% were Hispanic/Latino; and baseline ECOG performance status was 0 (54%) or 1 (46%). Sixty-three percent of patients had squamous cell carcinoma, 32% had adenocarcinoma, and 5% had adenosquamous histology. Ninety percent of patients had extrapelvic disease; 61% of patients had received 1 prior line of systemic therapy, and 38% had 2 prior lines of systemic therapy. All patients received prior chemotherapy; 64% received prior bevacizumab and 27% received prior anti-PD-1 or anti-PD-L1 therapy. Patients on the control arm received gemcitabine (44%), pemetrexed (32%), topotecan (8%), vinorelbine (7%), or irinotecan (6%).

Statistically significant improvements in OS, PFS, and ORR were demonstrated for TIVDAK compared with chemotherapy.

Table 9 and Figure 2 summarize the efficacy results from innovaTV 301.

Table 9. Efficacy Results in innovaTV 301
Endpoint | TIVDAK N=253 | Chemotherapy N=249
Overall Survival
Number (%) of patients with events | 123 (48.6) | 140 (56.2)
Median in months (95% CI) | 11.5 (9.8, 14.9) | 9.5 (7.9, 10.7)
Hazard ratio (95% CI) | 0.70 (0.54, 0.89)
p-value | 0.0038 [Based on a stratified log-rank test. The threshold for statistical significance is 0.0226 (2-sided)]
Progression Free Survival
Number (%) of patients with events | 198 (78.3) | 194 (77.9)
Median in months (95% CI) | 4.2 (4.0, 4.4) | 2.9 (2.6, 3.1)
Hazard ratio (95% CI) | 0.67 (0.54, 0.82)
p-value | <0.0001 [Based on a stratified log-rank test. The threshold for statistical significance is 0.0453 (2-sided)]
Confirmed Objective Response Rate (CR + PR)
ORR (%) (95% CI) | 17.8 (13.3, 23.1) | 5.2 (2.8, 8.8)
p-value | <0.0001 [Based on CMH test. The threshold for statistical significance is 0.05 (2-sided)]
Complete response rate (%) | 2.4 | 0
Partial response rate (%) | 15.4 | 5.2
CI: confidence interval

Figure 2. Kaplan Meier Plot of Overall Survival

innovaTV 204

The efficacy of TIVDAK was evaluated in innovaTV 204 (NCT03438396), an open-label, multicenter, single-arm trial that treated 101 patients with recurrent or metastatic cervical cancer who had received no more than two prior systemic regimens in the recurrent or metastatic setting, including at least one prior platinum-based chemotherapy regimen. Patients were excluded if they had active ocular surface disease, any prior episode of cicatricial conjunctivitis or ocular SJS, Grade ≥2 peripheral neuropathy or known coagulation defects leading to an increased risk of bleeding.

Patients received TIVDAK 2 mg/kg intravenously every 3 weeks until disease progression or unacceptable toxicity. Tumor response assessments were performed every 6 weeks for the first 30 weeks and every 12 weeks thereafter.

The median age was 50 years (range: 31 to 78); 95% were White, 2% were Asian, and 1% were Black. Six percent of patients were Hispanic or Latino. Sixty-eight percent of patients had squamous cell carcinoma, 27% had adenocarcinoma, and 5% had adenosquamous histology. ECOG performance status was 0 (58%) or 1 (42%). Seventy percent of patients had received 1 prior line of systemic therapy, and 30% had 2 prior lines of systemic therapy. Sixty-nine percent of patients previously received bevacizumab as part of their prior systemic therapy. Sixty-three percent received bevacizumab in combination with chemotherapy (paclitaxel and cisplatin or carboplatin, or paclitaxel and topotecan) as first-line therapy.

The major efficacy outcome measures were confirmed objective response rate (ORR) as assessed by an independent review committee (IRC) using RECIST v1.1 criteria and duration of response (DOR).

Efficacy results are presented in Table 10.

Table 10. Efficacy Results in innovaTV 204 by IRC
Endpoint | N=101
Confirmed ORR (95% CI) | 24% (15.9, 33.3)
Complete response rate | 7%
Partial response rate | 17%
Duration of Response
Median Duration of Response, months [Based on patients (n=24) with a response by IRC] (95% CI) | 8.3 (4.2, NR)
CI: confidence interval
NR: not reached

15 REFERENCES

1. “OSHA Hazardous Drugs.” OSHA. http://www.osha.gov/SLTC/hazardousdrugs/index.html

16 HOW SUPPLIED/STORAGE AND HANDLING

How Supplied

TIVDAK (tisotumab vedotin-tftv) is supplied as a white to off-white lyophilized cake or powder in a 40 mg single-dose vial for reconstitution. TIVDAK vials are available in the following packages:

- Carton of one 40 mg single-dose vial [NDC 51144-003-01]

Storage

Store TIVDAK vials refrigerated at 2ºC to 8ºC (36ºF to 46ºF) in the original carton to protect from light. Do not freeze. Do not shake.

Special Handling

TIVDAK is a hazardous drug. Follow special handling and disposal procedures.^1

17 PATIENT COUNSELING INFORMATION

Advise the patient to read the FDA-approved patient labeling (Medication Guide).

Ocular Adverse Reactions

- Inform patients about the eye exam they will receive with an eye care provider before starting TIVDAK, before each of the first nine cycles and as clinically indicated [see Warnings and Precautions (5.1)].
- Inform patients about the ocular signs or symptoms the eye care provider will review before each cycle [see Warnings and Precautions (5.1)].
- Inform patients that ocular adverse reactions may occur during treatment with TIVDAK and to contact their healthcare provider if they experience new or worsening ocular signs and symptoms [see Warnings and Precautions (5.1)].
- Instruct patients to bring their eye drops to each infusion and advise on how to administer the eye drops throughout treatment [see Dosage and Administration (2.2) and Warnings and Precautions (5.1)].
- Inform patients to avoid wearing contact lenses during treatment unless directed by an eye care provider [see Dosage and Administration (2.2)].

Peripheral Neuropathy

- Advise patients to report to their healthcare provider any numbness and tingling of the hands or feet or muscle weakness [see Warnings and Precautions (5.2)].

Hemorrhage

- Instruct patients to contact their healthcare provider to seek immediate medical attention for signs or symptoms of unusual severe bleeding or hemorrhage [see Warnings and Precautions (5.3)].

Pneumonitis

- Advise patients to immediately report new or worsening respiratory symptoms [see Warnings and Precautions (5.4)].

Severe Cutaneous Adverse Reactions

- Inform patients of the signs and symptoms of severe cutaneous adverse reactions, including life-threatening and potentially fatal SJS, which include target lesions, worsening skin reactions, blistering or peeling of the skin, painful sores in mouth, nose, throat, or genital area, fever or flu-like symptoms, and swollen lymph nodes [see Warnings and Precautions (5.5)].
- Instruct patients to contact their healthcare provider to seek immediate medical attention for signs or symptoms of severe cutaneous adverse reactions, including SJS [see Warnings and Precautions (5.5)].

Embryo-Fetal Toxicity

- Advise pregnant women and females of reproductive potential of the potential risk to the fetus. Advise patients to inform their healthcare providers of a known or suspected pregnancy [see Warnings and Precautions (5.6) and Use in Specific Populations (8.1)].
- Advise females of reproductive potential to use effective contraception during treatment and for 2 months after the last dose. Advise male patients with female partners of reproductive potential to use effective contraception during treatment and for 4 months after the last dose [see Use in Specific Populations (8.1, 8.3)].

Lactation

- Advise women not to breastfeed during treatment with TIVDAK and for 3 weeks after the last dose [see Use in Specific Populations (8.2)].

Manufactured by:
Seagen Inc.
Bothell, WA 98021
1-855-4SEAGEN

Marketed by:
Seagen Inc.
Bothell, WA 98021
and
Genmab US, Inc.
Plainsboro, NJ 08536

U.S. License 2257
TIVDAK® is a trademark owned by Seagen Inc.
©2025 Seagen Inc. and Genmab US, Inc.
LAB-1596-1.0

MEDICATION GUIDE

TIVDAK (TIV-dack)
(tisotumab vedotin-tftv)
for injection, for intravenous use

What is the most important information I should know about TIVDAK?
TIVDAK can cause serious side effects, including:
Eye problems. Eye problems are common with TIVDAK, and can also be severe. TIVDAK can cause changes to the surface of your eye that can lead to dry eyes, eye redness, eye irritation, corneal ulcers, blurred vision, and severe vision loss. Tell your healthcare provider if you develop new or worsening vision changes or eye problems during treatment with TIVDAK.

- Your healthcare provider will send you to an eye specialist to check your eyes before you start treatment with TIVDAK, before each infusion for your first 9 infusions of TIVDAK, and as needed for any new or worsening signs or symptoms of eye problems.
- Your healthcare provider will ask if you have any signs or symptoms of eye problems before each infusion. You will be referred to an eye specialist for any new or worsening signs or symptoms of eye problems.
- Your healthcare provider will prescribe 3 different types of eye drops before you start treatment with TIVDAK. Bring the eye drops with you to each infusion and use them as directed by your healthcare provider to reduce your risk of eye problems:
  - Use 1 drop of steroid eye drops in each eye before each infusion and continue to use your eye drops 3 times a day for 3 days after each infusion.
  - Use vasoconstrictor eye drops right before each infusion.
  - Use lubricating eye drops throughout treatment and for 30 days after your last dose of TIVDAK.
- Do not wear contact lenses throughout your treatment with TIVDAK unless you are told to use them by your eye specialist.

See “What are the possible side effects of TIVDAK?” for more information about side effects.

What is TIVDAK?
TIVDAK is a prescription medicine used to treat adults with cervical cancer:

- that has returned or has spread to other parts of the body, and
- who have received chemotherapy that did not work or is no longer working.

It is not known if TIVDAK is safe and effective in children.

Before receiving TIVDAK, tell your healthcare provider about all of your medical conditions, including if you:

- have a history of vision or eye problems
- have numbness or tingling in your hands or feet
- have bleeding problems
- have liver problems
- are pregnant or plan to become pregnant. TIVDAK can harm your unborn baby. Tell your healthcare provider right away if you become pregnant or think you may be pregnant during treatment with TIVDAK.
  Females who are able to become pregnant:
  - Your healthcare provider should do a pregnancy test before you start treatment with TIVDAK.
  - You should use an effective birth control during treatment and for 2 months after your last dose of TIVDAK.
Males with female partners who are able to become pregnant:
  1. You should use an effective birth control during treatment and for 4 months after your last dose of TIVDAK.
- are breastfeeding or plan to breastfeed. It is not known if TIVDAK passes into your breast milk. Do not breastfeed during treatment and for 3 weeks after your last dose of TIVDAK.

Tell your healthcare provider about all the medicines you take, including prescription and over-the-counter medicines, vitamins, and herbal supplements. Taking TIVDAK with certain other medicines may cause side effects.

How will I receive TIVDAK?

- TIVDAK will be given to you by intravenous (IV) infusion into your vein over 30 minutes.
- TIVDAK is usually given every 3 weeks.
- Your healthcare provider will decide how many infusions you need.
- Your healthcare provider will put cold packs on your eyes during each infusion.
- Your healthcare provider may decrease your dose, temporarily stop, or completely stop treatment with TIVDAK if you have side effects.

What are the possible side effects of TIVDAK?
TIVDAK can cause serious side effects, including:

- See “What is the most important information I should know about TIVDAK?”
- Peripheral neuropathy. Nerve problems called peripheral neuropathy are common with TIVDAK, and can also be serious. Tell your healthcare provider right away if you get numbness or tingling in your hands or feet or muscle weakness.
- Bleeding (hemorrhage). Bleeding problems are common with TIVDAK, and can also be serious. Tell your healthcare provider or get medical help right away if you get signs or symptoms of bleeding during treatment with TIVDAK, including:

- blood in your stools or black stools (looks like tar)
- blood in your urine
- cough up or vomit blood

- unusual vaginal bleeding
- any unusual or heavy bleeding

- Lung problems. TIVDAK may cause severe or life-threatening inflammation of the lungs that can lead to death. Tell your healthcare provider right away if you get new or worsening symptoms, including trouble breathing, shortness of breath, or cough.
- Severe skin reactions. TIVDAK may cause severe or life-threatening skin reactions that can lead to death. Tell your healthcare provider or get medical help right away if you get signs or symptoms of a severe skin reaction during treatment with TIVDAK, including:

- skin reactions that look like rings (target lesions)
- rash or itching that continues to get worse
- blistering or peeling of the skin
- painful sores or ulcers in your mouth, nose, throat, or genital area

- fever or flu-like symptoms
- swollen lymph nodes

The most common side effects of TIVDAK include:

- decreased red blood cell counts
- numbness or tingling in your hands or feet
- eye problems (conjunctival disorders)

- nausea
- tiredness
- changes in liver function blood tests

- nosebleed
- hair loss (alopecia)
- bleeding (hemorrhage)

TIVDAK may cause fertility problems in females and males, which may affect your ability to have children. Talk to your healthcare provider if this is a concern for you.
These are not all of the possible side effects of TIVDAK.
Call your doctor for medical advice about side effects. You may report side effects to FDA at 1-800-FDA-1088.

General information about the safe and effective use of TIVDAK.
Medicines are sometimes prescribed for purposes other than those listed in a Medication Guide. If you would like more information about TIVDAK, talk with your healthcare provider. You can ask your pharmacist or healthcare provider for information about TIVDAK that is written for healthcare professionals.

What are the ingredients in TIVDAK?
Active ingredient: tisotumab vedotin-tftv
Inactive ingredients: d-mannitol, l-histidine, l-histidine monohydrochloride, and sucrose.
Manufactured by: Seagen Inc., Bothell, WA 98021
Marketed by: Seagen Inc., Bothell, WA 98021 and Genmab US, Inc., Plainsboro, NJ 08536
U.S. License 2257
TIVDAK® is a trademark owned by Seagen Inc.
©2025 Seagen Inc. and Genmab US, Inc.
LAB-1597-1.0
For more information, go to www.tivdak.com or call 1-855-4SEAGEN

This Medication Guide has been approved by the U.S. Food and Drug Administration. Revised: 11/2025

PRINCIPAL DISPLAY PANEL

Rx Only
NDC 51144-003-01
tivdak®
(tisotumab vedotin-tftv)
for injection
40 mg/vial
CAUTION: Hazardous Agent
For intravenous infusion only
Must reconstitute and dilute before use
One single-dose vial.
Discard unused portion.
Provide the enclosed
Medication Guide to each patient
Seagen®
Genmab
Dosage:
See Prescribing Information.
Storage:
Store vial refrigerated at
2ºC to 8ºC (36ºF to 46ºF) in
original carton to protect from
light. DO NOT FREEZE.
DO NOT SHAKE.
No U.S. Standard of Potency
U.S. License 2257
TIVDAK and the TIVDAK logo
are US registered trademarks
owned by Seagen Inc.
Seagen is US registered
trademark of Seagen Inc.
©2021 Seagen Inc. and Genmab.
All rights reserved.
Printed in USA
PRODUCT OF SWITZERLAND
Each vial contains 40 mg of
tisotumab vedotin-tftv.
No Preservative
After reconstitution with
4 mL of Sterile Water for
Injection, USP, the
concentration of TIVDAK
(tisotumab vedotin-tftv) is
10 mg/mL
Each mL of reconstituted
solution contains 10 mg of
tisotumab vedotin-tftv,
D-mannitol (30 mg),
L-histidine (2.11 mg),
L-histidine monojhydrochloride
(3.44 mg), and sucrose (30mg)
Mfg by:
Seagen Inc.
Bothell, WA 98021
For more information:
1-855-4SEAGEN
GTIN 00351144003014
1401 - 02

Rx Only
NDC 51144-003-01
tivdak®
(tisotumab vedotin-tftv)
for injection
40 mg/vial
For intravenous infusion only
Must reconstitute and dilute before use
Single-dose vial. Discard unused portion.
CAUTION: Hazardous Agent
Store at 2ºC to 8ºC (36ºF to 46ºF)
Protect from light.
DO NOT FREEZE. DO NOT SHAKE.
Dosage: See Prescribing Information
Provide the enclosed Medication Guide to each patient.
Mfg by: Seagen Inc. U.S. License 2257
PRODUCT OF SWITZERLAND
Seagen®
Genmab
1400-02